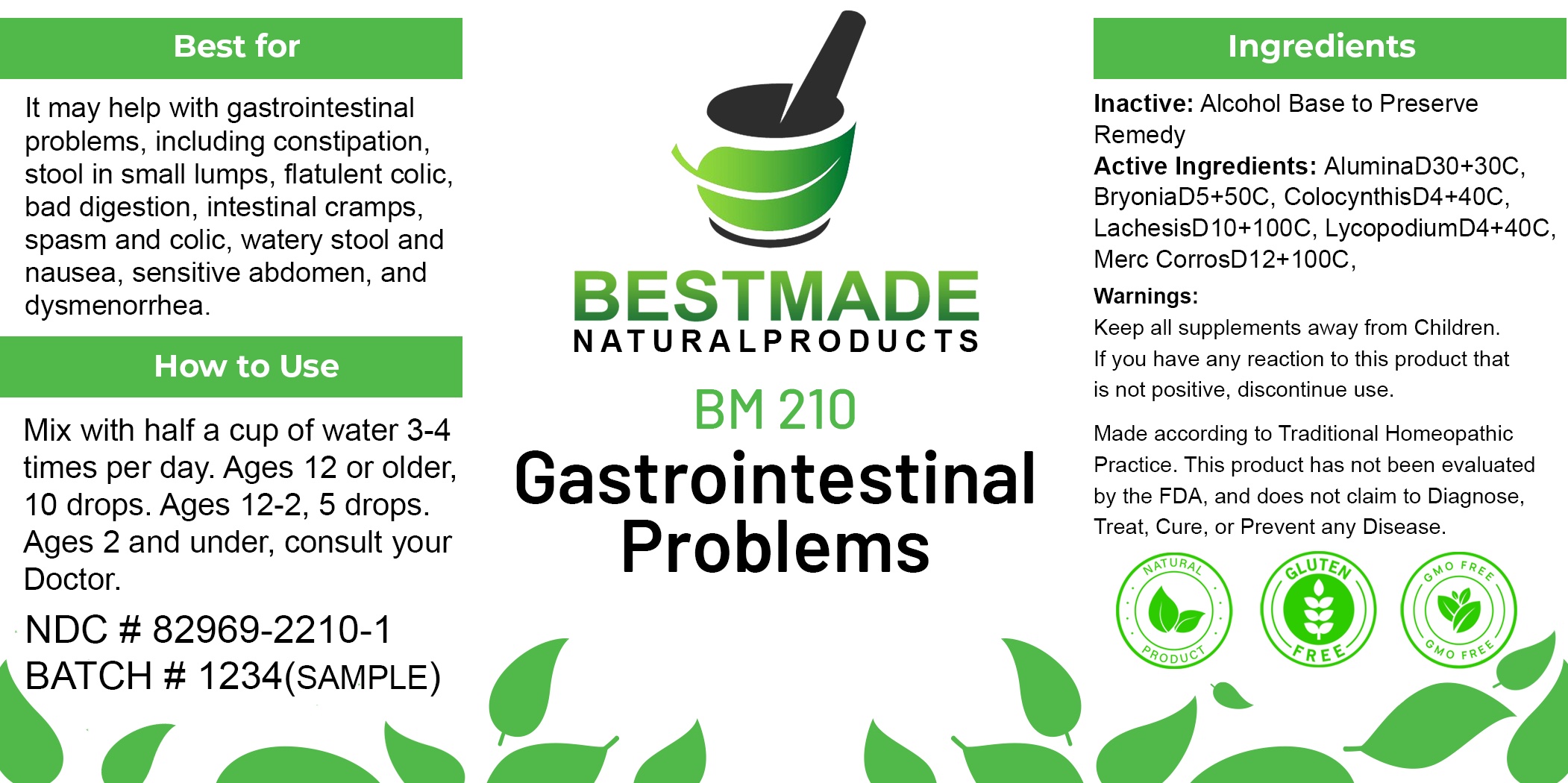 DRUG LABEL: Bestmade Natural Products BM210
NDC: 82969-2210 | Form: LIQUID
Manufacturer: Bestmade Natural Products
Category: homeopathic | Type: HUMAN OTC DRUG LABEL
Date: 20241218

ACTIVE INGREDIENTS: LACHESIS MUTA WHOLE 30 [hp_C]/30 [hp_C]; STRYCHNOS NUX-VOMICA SEED 30 [hp_C]/30 [hp_C]; MERCURIC CHLORIDE 30 [hp_C]/30 [hp_C]; ALUMINUM OXIDE 30 [hp_C]/30 [hp_C]; BRYONIA ALBA ROOT 30 [hp_C]/30 [hp_C]; CITRULLUS COLOCYNTHIS FRUIT PULP 30 [hp_C]/30 [hp_C]; LYCOPODIUM CLAVATUM SPORE 30 [hp_C]/30 [hp_C]
INACTIVE INGREDIENTS: ALCOHOL 30 [hp_C]/30 [hp_C]

DOSAGE AND ADMINISTRATION

How to Use
Take with water 3-4 times a day.
Ages 12 or older, 5 Pellets,
Ages 12-2, 3 Pellets, Ages
below 2, consult your Doctor.

INDICATIONS AND USAGE

It may help with gastrointestinal problems, including constipation, stool in small lumps, flatulent colic, bad digestion, intestinal cramps, spasm and colic, watery stool and nausea, sensitive abdomen, and dysmenorrhea.

PURPOSE

It may help with gastrointestinal problems, including constipation, stool in small lumps, flatulent colic, bad digestion, intestinal cramps, spasm and colic, watery stool and nausea, sensitive abdomen, and dysmenorrhea.

INACTIVE INGREDIENT

Alcohol base to preserve product.

ACTIVE INGREDIENTS

AluminaD30+30C, BryoniaD5+50C, ColocynthisD4+40C, LachesisD10+100C, LycopodiumD4+40C, Merc CorrosD12+100C, Nux VomicaD6+60C

Warnings:
Keep all supplements away from Children.
If you have any reaction to this product that is not positive, discontinue use.

Made according to Traditional Homeopathic Practice. This product has not been evaluated by the FDA, and does not claim to Diagnose, Treat, Cure, or Prevent any Disease.

Warnings:
Keep all supplements away from Children.
If you have any reaction to this product that is not positive, discontinue use.

Made according to Traditional Homeopathic Practice. This product has not been evaluated by the FDA, and does not claim to Diagnose, Treat, Cure, or Prevent any Disease.

Entire Package Label.